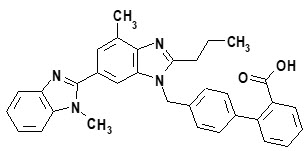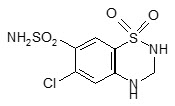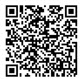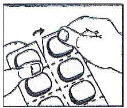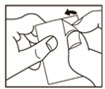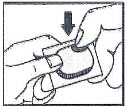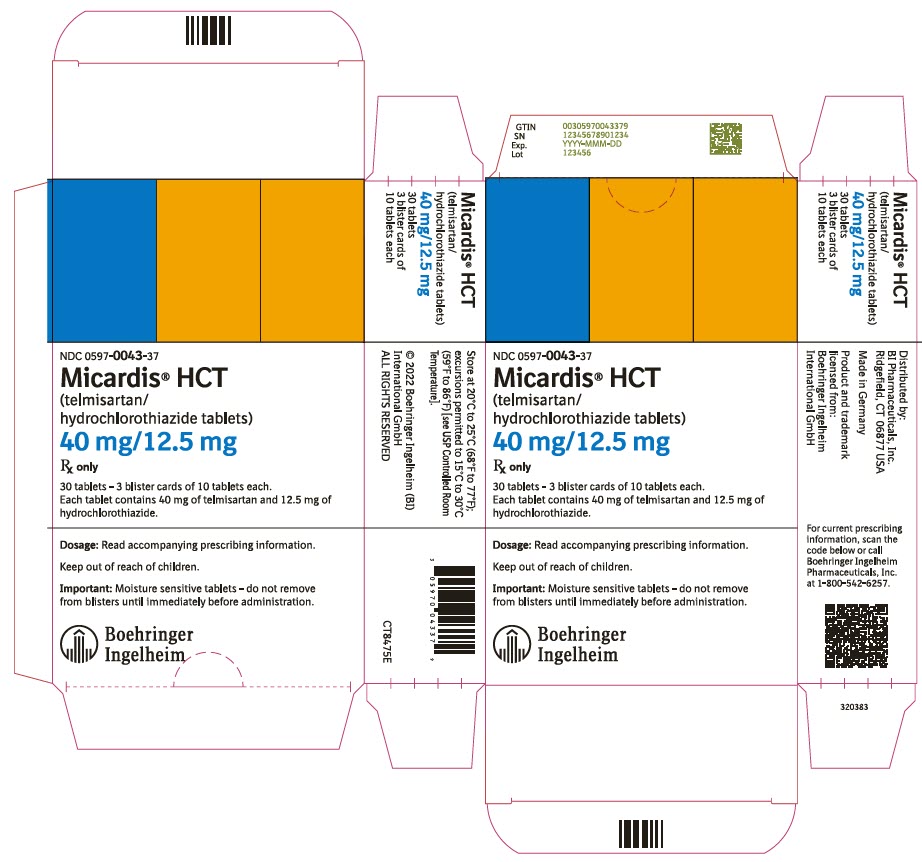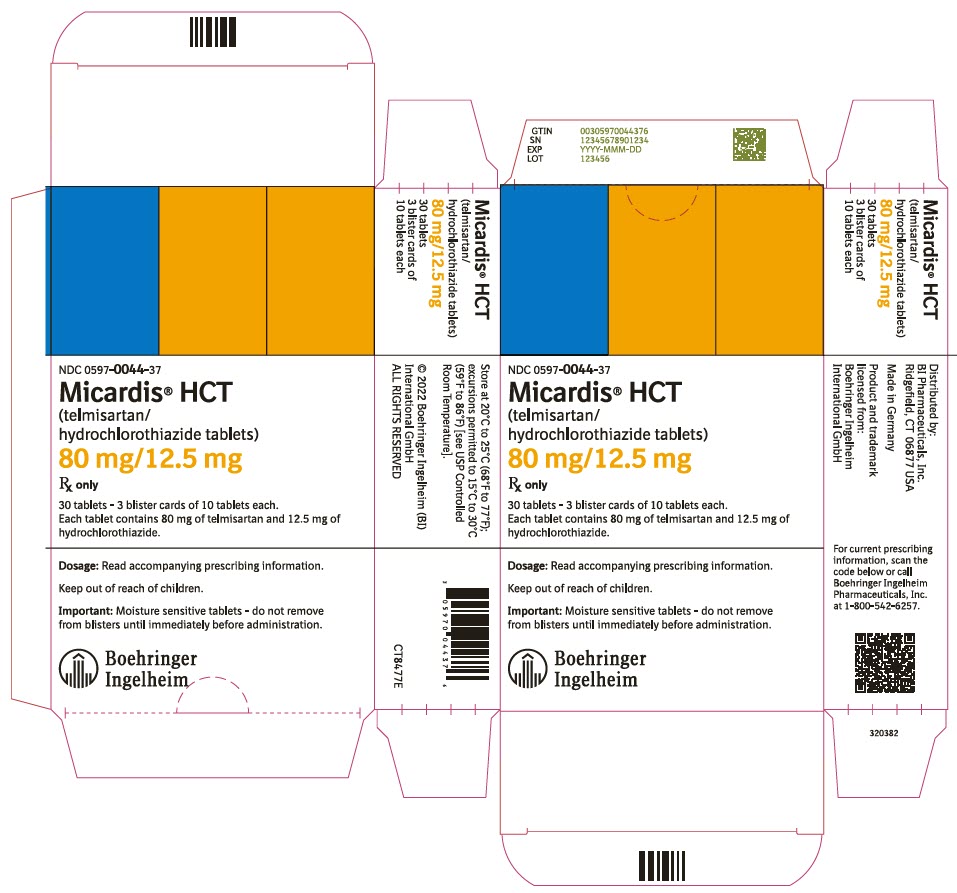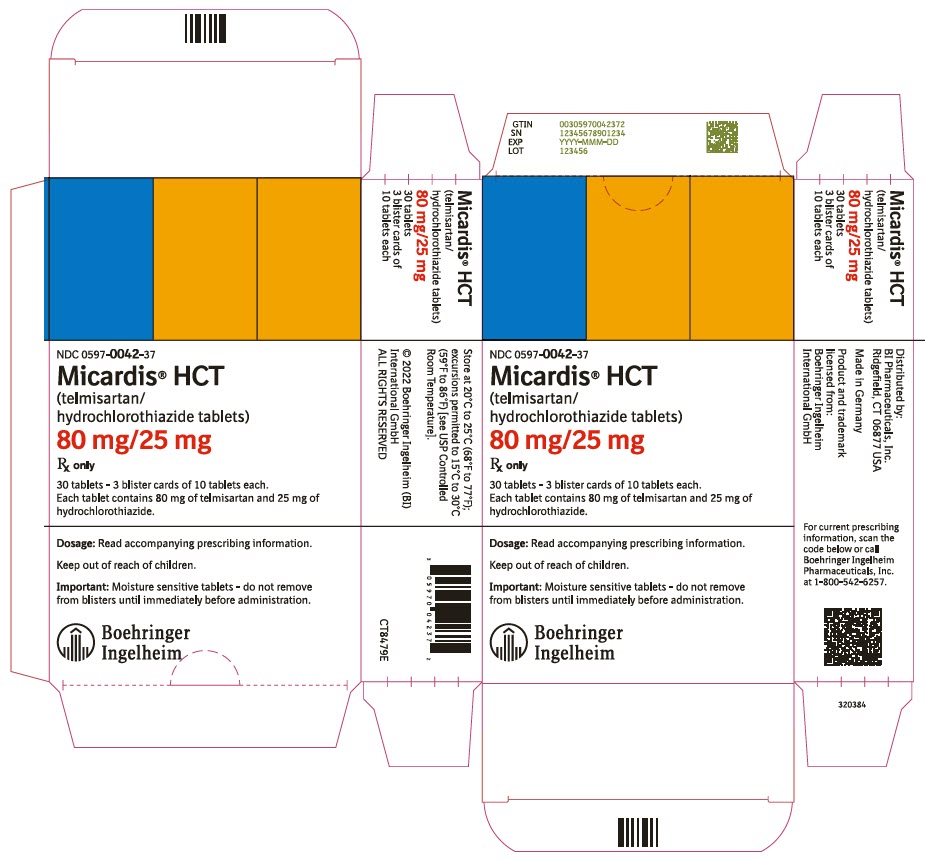 DRUG LABEL: Micardis HCT
NDC: 0597-0043 | Form: TABLET
Manufacturer: Boehringer Ingelheim Pharmaceuticals, Inc.
Category: prescription | Type: HUMAN PRESCRIPTION DRUG LABEL
Date: 20241231

ACTIVE INGREDIENTS: TELMISARTAN 40 mg/1 1; HYDROCHLOROTHIAZIDE 12.5 mg/1 1

HIGHLIGHTS OF PRESCRIBING INFORMATION

These highlights do not include all the information needed to use MICARDIS HCT safely and effectively. See full prescribing information for MICARDIS HCT.
MICARDIS® HCT (telmisartan and hydrochlorothiazide tablets), for oral use
Initial U.S. Approval: 2000

WARNING: FETAL TOXICITY

See full prescribing information for complete boxed warning.

- When pregnancy is detected, discontinue MICARDIS HCT as soon as possible. (5.1, 8.1)
- Drugs that act directly on the renin-angiotensin system can cause injury and death to the developing fetus. (5.1, 8.1)

1 INDICATIONS AND USAGE

- MICARDIS HCT is a combination of an angiotensin II receptor blocker (ARB) and a thiazide diuretic indicated for the treatment of hypertension, alone or with other antihypertensive agents, to lower blood pressure. Lowering blood pressure reduces the risk of fatal and nonfatal cardiovascular events, primarily strokes and myocardial infarctions. (1)
- MICARDIS HCT is not indicated for initial therapy (1)

2 DOSAGE AND ADMINISTRATION

- Usual starting dose is 80 mg/12.5 mg once daily (2.1)
- Titrate up to 160 mg/25 mg as needed (2.1)
- Initiate patients with biliary obstructive disorders or hepatic insufficiency at 40 mg/12.5 mg (2.2)

3 DOSAGE FORMS AND STRENGTHS

Tablets: 40 mg/12.5 mg, 80 mg/12.5 mg, 80 mg/25 mg (3)

4 CONTRAINDICATIONS

- Hypersensitivity to telmisartan or any component (4)
- Anuria (4)
- Co-Administration with aliskiren in patients with diabetes (4)

5 WARNINGS AND PRECAUTIONS

- Avoid fetal or neonatal exposure (5.1)
- Correct volume or salt depletion before initiating therapy. Observe for signs and symptoms of hypotension. (5.2)
- Monitor renal function and potassium in susceptible patients (5.3)
- Observe for clinical signs of fluid or electrolyte imbalance (5.4)
- Hypersensitivity Reaction (5.5)
- Acute Myopia and Secondary Angle-Closure Glaucoma (5.6)

6 ADVERSE REACTIONS

The most common adverse reactions (≥2% of patients) were upper respiratory tract infection, dizziness, sinusitis, diarrhea, fatigue, influenza-like symptoms, and nausea (6.1)

To report SUSPECTED ADVERSE REACTIONS, contact Boehringer Ingelheim Pharmaceuticals, Inc. at (800) 542-6257 or FDA at 1-800-FDA-1088 or www.fda.gov/medwatch.

7 DRUG INTERACTIONS

- Lithium: Risk of lithium toxicity (7.2)
- Non-steroidal anti-inflammatory drugs (NSAIDs): Reduced diuretic, natriuretic, and antihypertensive effects; increased risk of renal impairment (7.3)
- Dual blockade of renin-angiotensin system: Increased risk of renal impairment, hypotension, and hyperkalemia (7.4)
- Antidiabetic drugs: Dosage adjustment may be required (7.6)
- Cholestyramine and colestipol: Reduced absorption of thiazides (7.7)

8 USE IN SPECIFIC POPULATIONS

- Lactation: Do not breastfeed during treatment with MICARDIS HCT (8.2)
- Severe Hepatic Impairment: Use not recommended (8.6)
- Severe Renal Impairment: Use not recommended (8.7)

FULL PRESCRIBING INFORMATION

WARNING: FETAL TOXICITY

- When pregnancy is detected, discontinue MICARDIS HCT as soon as possible [see Warnings and Precautions (5.1) and Use in Specific Populations (8.1)].
- Drugs that act directly on the renin-angiotensin system can cause injury and death to the developing fetus [see Warnings and Precautions (5.1) and Use in Specific Populations (8.1)].

1 INDICATIONS AND USAGE

MICARDIS HCT (telmisartan and hydrochlorothiazide) is indicated for the treatment of hypertension, to lower blood pressure. Lowering blood pressure reduces the risk of fatal and nonfatal cardiovascular events, primarily strokes and myocardial infarctions. These benefits have been seen in controlled trials of antihypertensive drugs from a wide variety of pharmacologic classes including the classes to which this drug principally belongs. There are no controlled trials demonstrating risk reduction with MICARDIS HCT.

Control of high blood pressure should be part of comprehensive cardiovascular risk management, including, as appropriate, lipid control, diabetes management, antithrombotic therapy, smoking cessation, exercise, and limited sodium intake. Many patients will require more than one drug to achieve blood pressure goals. For specific advice on goals and management, see published guidelines, such as those of the National High Blood Pressure Education Program's Joint National Committee on Prevention, Detection, Evaluation, and Treatment of High Blood Pressure (JNC).

Numerous antihypertensive drugs, from a variety of pharmacologic classes and with different mechanisms of action, have been shown in randomized controlled trials to reduce cardiovascular morbidity and mortality, and it can be concluded that it is blood pressure reduction, and not some other pharmacologic property of the drugs, that is largely responsible for those benefits. The largest and most consistent cardiovascular outcome benefit has been a reduction in the risk of stroke, but reductions in myocardial infarction and cardiovascular mortality also have been seen regularly.

Elevated systolic or diastolic pressure causes increased cardiovascular risk, and the absolute risk increase per mmHg is greater at higher blood pressures, so that even modest reductions of severe hypertension can provide substantial benefit. Relative risk reduction from blood pressure reduction is similar across populations with varying absolute risk, so the absolute benefit is greater in patients who are at higher risk independent of their hypertension (for example, patients with diabetes or hyperlipidemia), and such patients would be expected to benefit from more aggressive treatment to a lower blood pressure goal.

Some antihypertensive drugs have smaller blood pressure effects (as monotherapy) in black patients, and many antihypertensive drugs have additional approved indications and effects (e.g., on angina, heart failure, or diabetic kidney disease). These considerations may guide selection of therapy [see Clinical Studies (14)].

MICARDIS HCT is not indicated for initial therapy for the treatment of hypertension [see Dosage and Administration (2.1)].

MICARDIS HCT may be used alone or in combination with other antihypertensive agents.

2 DOSAGE AND ADMINISTRATION

2.1 Dosing Information

Initiate a patient whose blood pressure is not adequately controlled with telmisartan monotherapy 80 mg on MICARDIS HCT, 80 mg/12.5 mg orally once daily. Dose can be titrated up to 160 mg/25 mg after 2 to 4 weeks, if necessary.

Initiate a patient whose blood pressure is not adequately controlled by 25 mg once daily of hydrochlorothiazide, or is controlled but who experiences hypokalemia with this regimen on MICARDIS HCT 80 mg/12.5 mg once daily. Dose can be titrated up to 160 mg/25 mg after 2 to 4 weeks, if necessary.

Patients titrated to the individual components (telmisartan and hydrochlorothiazide) may instead receive the corresponding dose of MICARDIS HCT.

MICARDIS HCT may be administered with other antihypertensive drugs.

2.2 Dose Adjustment for Hepatic Impairment

Initiate patients with biliary obstructive disorders or hepatic insufficiency under close medical supervision using the 40 mg/12.5 mg combination. MICARDIS HCT tablets are not recommended for patients with severe hepatic impairment [see Use in Specific Populations (8.6) and Clinical Pharmacology (12.3)].

2.3 Important Administration Instructions

MICARDIS HCT tablets should not be removed from blisters until immediately before administration.

3 DOSAGE FORMS AND STRENGTHS

- 40 mg/12.5 mg, red and white tablets marked with the Boehringer Ingelheim logo and "H4"
- 80 mg/12.5 mg, red and white tablets marked with the Boehringer Ingelheim logo and "H8"
- 80 mg/25 mg, yellow and white tablets marked with the Boehringer Ingelheim logo and "H9"

4 CONTRAINDICATIONS

MICARDIS HCT is contraindicated:

- In patients who are hypersensitive to any component of this product [see Warnings and Precautions (5.5)].
- In patients with anuria.
- For co-administration with aliskiren in patients with diabetes [see Drug Interactions (7.4)].

5 WARNINGS AND PRECAUTIONS

5.1 Fetal Toxicity

Telmisartan

Use of drugs that act on the renin-angiotensin system during the second and third trimesters of pregnancy reduces fetal renal function and increases fetal and neonatal morbidity and death. Resulting oligohydramnios can be associated with fetal lung hypoplasia and skeletal deformations. Potential neonatal adverse effects include skull hypoplasia, anuria, hypotension, renal failure, and death. When pregnancy is detected, discontinue MICARDIS HCT as soon as possible.

Hydrochlorothiazide

Thiazides cross the placental barrier and appear in cord blood. Adverse reactions include fetal or neonatal jaundice and thrombocytopenia [see Use in Specific Populations (8.1)].

5.2 Hypotension in Volume- or Salt-Depleted Patients

In patients with an activated renin-angiotensin system, such as volume- or salt-depleted patients (e.g., those being treated with high doses of diuretics), symptomatic hypotension may occur after initialization of treatment with MICARDIS HCT. Correct volume or salt depletion prior to administration of MICARDIS HCT.

5.3 Impaired Renal Function

Changes in renal function including acute renal failure can be caused by drugs that inhibit the renin-angiotensin system and by diuretics. Patients whose renal function may depend in part on the activity of the renin-angiotensin system (e.g., patients with renal artery stenosis, chronic kidney disease, severe congestive heart failure, or volume depletion) may be at particular risk of developing oliguria, progressive azotemia, or acute renal failure on MICARDIS HCT. Monitor renal function periodically in these patients. Consider withholding or discontinuing therapy in patients who develop a clinically significant decrease in renal function on MICARDIS HCT.

5.4 Electrolytes and Metabolic Disorders

Drugs, including telmisartan, that inhibit the renin-angiotensin system can cause hyperkalemia, particularly in patients with renal insufficiency, diabetes, or combination use with other angiotensin receptor blockers or ACE inhibitors and the concomitant use of other drugs that raise serum potassium levels [see Drug Interactions (7.1, 7.4)].

Hydrochlorothiazide can cause hypokalemia and hyponatremia. Thiazides have been shown to increase the urinary excretion of magnesium; this may result in hypomagnesemia. Hypomagnesemia can result in hypokalemia which may be difficult to treat despite potassium repletion. Monitor serum electrolytes periodically.

In controlled trials using the telmisartan/hydrochlorothiazide combination treatment, no patient administered 40 mg/12.5 mg, 80 mg/12.5 mg, or 80 mg/25 mg experienced a decrease in potassium ≥1.4 mEq/L, and no patient experienced hyperkalemia.

Hydrochlorothiazide decreases urinary calcium excretion and may cause elevations of serum calcium.

Hydrochlorothiazide may alter glucose tolerance and raise serum levels of cholesterol and triglycerides.

Hyperuricemia may occur or frank gout may be precipitated in certain patients receiving thiazide therapy. Because telmisartan decreases uric acid, telmisartan in combination with hydrochlorothiazide attenuates the diuretic-induced hyperuricemia.

5.5 Hypersensitivity Reaction

Hydrochlorothiazide

Hypersensitivity reactions to hydrochlorothiazide may occur in patients with or without a history of allergy or bronchial asthma, but are more likely in patients with such a history [see Contraindications (4)].

5.6 Acute Myopia and Secondary Angle-Closure Glaucoma

Hydrochlorothiazide, a sulfonamide, can cause an idiosyncratic reaction, resulting in acute transient myopia and acute angle-closure glaucoma. Symptoms include acute onset of decreased visual acuity or ocular pain and typically occur within hours to weeks of drug initiation. Untreated acute angle-closure glaucoma can lead to permanent vision loss. The primary treatment is to discontinue hydrochlorothiazide as rapidly as possible. Prompt medical or surgical treatments may need to be considered if the intraocular pressure remains uncontrolled. Risk factors for developing acute angle-closure glaucoma may include a history of sulfonamide or penicillin allergy.

5.7 Systemic Lupus Erythematosus

Thiazide diuretics have been reported to cause exacerbation or activation of systemic lupus erythematosus.

5.8 Postsympathectomy Patients

The antihypertensive effects of hydrochlorothiazide may be enhanced in the postsympathectomy patient.

6 ADVERSE REACTIONS

The following adverse reactions are discussed elsewhere in labeling:

- Hypotension [see Warnings and Precautions (5.2)]
- Renal Impairment [see Warnings and Precautions (5.3)]
- Electrolytes and Metabolic Disorders [see Warnings and Precautions (5.4)]

6.1 Clinical Trials Experience

Because clinical studies are conducted under widely varying conditions, adverse reaction rates observed in the clinical studies of a drug cannot be directly compared to rates in the clinical studies of another drug and may not reflect the rates observed in practice.

MICARDIS HCT has been evaluated for safety in more than 1700 patients, including 716 treated for hypertension for longer than 6 months and 420 for more than 1 year. Adverse reactions have been limited to those that have been previously reported with telmisartan and/or hydrochlorothiazide.

Adverse reactions occurring at an incidence of ≥2% in patients treated with telmisartan/hydrochlorothiazide and at a greater rate than in patients treated with placebo, are presented in Table 1 [see Clinical Studies (14)].

Table 1 Adverse Reactions Occurring at an Incidence of ≥2% in Patients Treated with Telmisartan/Hydrochlorothiazide and at a Greater Rate Than in Patients Treated with Placebo*
 | Telmisartan/Hydrochlorothiazide (n = 414) | Placebo (n = 74) | Telmisartan (n = 209) | Hydrochlorothiazide (n = 121)
Body as a whole
Fatigue | 3% | 1% | 3% | 3%
Influenza-like symptoms | 2% | 1% | 2% | 3%
Central/Peripheral nervous system Dizziness | 5% | 1% | 4% | 6%
Gastrointestinal system
Diarrhea | 3% | 0% | 5% | 2%
Nausea | 2% | 0% | 1% | 2%
Respiratory system disorder Sinusitis | 4% | 3% | 3% | 6%
Upper respiratory tract infection | 8% | 7% | 7% | 10%
* includes all doses of telmisartan (20 to 160 mg), hydrochlorothiazide (6.25 to 25 mg), and combinations thereof

Other adverse reactions observed for telmisartan/hydrochlorothiazide were: pain (including back and abdominal), dyspepsia, erythema, vomiting, bronchitis, and pharyngitis.

Adverse reactions occurred at approximately the same rates in men and women, older and younger patients, and black and non-black patients.

Telmisartan

Other adverse events that have been reported with telmisartan are listed below:

Autonomic Nervous System: impotence, increased sweating, flushing

Body as a Whole: allergy, fever, leg pain, chest pain

Cardiovascular: palpitation, angina pectoris, abnormal ECG, hypertension, peripheral edema

Central Nervous System: insomnia, somnolence, migraine, paresthesia, involuntary muscle contractions, hypoesthesia

Gastrointestinal: flatulence, constipation, gastritis, dry mouth, hemorrhoids, gastroesophageal reflux, toothache

Hepato-biliary: elevations of liver enzymes or serum bilirubin

Metabolic: gout, hypercholesterolemia, diabetes mellitus

Musculoskeletal: arthritis, arthralgia, leg cramps, myalgia

Psychiatric: anxiety, depression, nervousness

Resistance Mechanism: infection, abscess, otitis media

Respiratory: asthma, rhinitis, dyspnea, epistaxis

Skin: dermatitis, eczema, pruritus

Urinary: micturition frequency, cystitis

Vascular: cerebrovascular disorder

Special Senses: abnormal vision, conjunctivitis, tinnitus, earache

Hydrochlorothiazide

Other adverse events that have been reported with hydrochlorothiazide are listed below:

Body as a Whole: weakness

Digestive: pancreatitis, jaundice (intrahepatic cholestatic jaundice), sialadenitis, cramping, gastric irritation

Hematologic: aplastic anemia, agranulocytosis, leukopenia, hemolytic anemia, thrombocytopenia

Hypersensitivity: purpura, photosensitivity, urticaria, necrotizing angiitis (vasculitis and cutaneous vasculitis), fever, respiratory distress including pneumonitis and pulmonary edema, anaphylactic reactions

Metabolic: hyperglycemia, glycosuria

Musculoskeletal: muscle spasm

Nervous System/Psychiatric: restlessness

Renal: interstitial nephritis

Skin: erythema multiforme including Stevens-Johnson syndrome, exfoliative dermatitis including toxic epidermal necrolysis

Special Senses: transient blurred vision, xanthopsia

Clinical Laboratory Findings

Creatinine, Blood Urea Nitrogen (BUN): Increases in BUN (≥11.2 mg/dL) and serum creatinine (≥0.5 mg/dL) were observed in 2.8% and 1.4%, respectively, of patients with essential hypertension treated with MICARDIS HCT tablets in controlled trials. No patient discontinued treatment with MICARDIS HCT tablets because of an increase in BUN or creatinine [see Warnings and Precautions (5.3)].

6.2 Postmarketing Experience

The following adverse reactions have been identified during post-approval use of MICARDIS HCT. Because these reactions are reported voluntarily from a population of uncertain size, it is not always possible to estimate reliably their frequency or establish a causal relationship to drug exposure.

Blood and Lymphatic System Disorders: Eosinophilia

Cardiac Disorders: Tachycardia

Ear and Labyrinth Disorders: Vertigo

General Disorders and Administration Site Conditions: Asthenia, edema

Hepato-biliary: Abnormal hepatic function/liver disorder

Immune System Disorders: Anaphylactic reaction

Investigations: Increased CPK

Metabolism and Nutrition Disorders: Hypoglycemia (in diabetic patients), hyponatremia

Musculoskeletal and Connective Tissue Disorders: Rhabdomyolysis

Nervous System Disorders: Headache, syncope

Renal and Urinary Disorders: Renal failure, renal impairment including acute renal failure

Reproductive System and Breast Disorders: Erectile dysfunction

Respiratory, Thoracic and Mediastinal Disorders: Coughing

Skin and Subcutaneous Tissue Disorders: Angioedema (with fatal outcome), drug eruption (toxic skin eruption mostly reported as toxicoderma, rash, and urticaria)

Vascular Disorder: Orthostatic hypotension

Non-melanoma Skin Cancer

Hydrochlorothiazide is associated with an increased risk of non-melanoma skin cancer. In a study conducted in the Sentinel System, increased risk was predominantly for squamous cell carcinoma (SCC) and in white patients taking large cumulative doses. The increased risk for SCC in the overall population was approximately 1 additional case per 16,000 patients per year, and for white patients taking a cumulative dose of ≥50,000 mg the risk increase was approximately 1 additional SCC case for every 6,700 patients per year.

7 DRUG INTERACTIONS

7.1 Agents Increasing Serum Potassium

Co-administration of telmisartan with other drugs that raise serum potassium levels may result in hyperkalemia. Monitor serum potassium in such patients.

7.2 Lithium

Increases in serum lithium concentrations and lithium toxicity have been reported with concomitant use of thiazide diuretics or angiotensin II receptor antagonists, including telmisartan. Monitor lithium levels in patients receiving MICARDIS HCT and lithium.

7.3 Non-Steroidal Anti-Inflammatory Agents including Selective Cyclooxygenase-2 Inhibitors

Telmisartan

Non-Steroidal Anti-Inflammatory Agents including Selective Cyclooxygenase-2 Inhibitors (COX-2 Inhibitors): In patients who are elderly, volume-depleted (including those on diuretic therapy), or with compromised renal function, co-administration of NSAIDs, including selective COX-2 inhibitors, with ARBs, including telmisartan, may result in deterioration of renal function, including possible acute renal failure. These effects are usually reversible. The antihypertensive effect of ARBs may be attenuated by NSAIDs. Therefore, monitor renal function and blood pressure periodically in patients receiving MICARDIS HCT and NSAIDs.

Hydrochlorothiazide

Administration of a non-steroidal anti-inflammatory agent, including a selective COX-2 inhibitor, can reduce the diuretic, natriuretic, and antihypertensive effects of diuretics. Therefore, when MICARDIS HCT and non-steroidal anti-inflammatory agents including selective COX-2 inhibitors are used concomitantly, observe closely to determine if the desired effect of the diuretic is obtained.

7.4 Dual Blockade of the Renin-Angiotensin-Aldosterone System and Changes in Renal Function

Dual blockade of the renin-angiotensin-aldosterone system (RAS) with angiotensin blockers, ACE inhibitors, or aliskiren is associated with increased risks of hypotension, hyperkalemia, and renal impairment. The ONTARGET trial enrolled 25,620 patients ≥55 years old with atherosclerotic disease or diabetes with end-organ damage, randomizing them to telmisartan (ARB) only, ramipril (ACE inhibitor) only, or the combination, and followed them for a median of 56 months. Patients who received the combination of ARB and ACE inhibitor did not obtain any additional benefit (no additional reduction of risk of cardiovascular death, myocardial infarction, stroke, or hospitalization from heart failure) compared to ARB monotherapy or ACE inhibitor monotherapy, but experienced an increased incidence of renal dysfunction (e.g., acute renal failure) compared with monotherapy groups.

In general, avoid combined use of RAS inhibitors. Closely monitor blood pressure, renal function and electrolytes in patients on MICARDIS HCT and other agents that affect the RAS.

Do not co-administer aliskiren with MICARDIS HCT in patients with diabetes. Avoid concomitant use of aliskiren with MICARDIS HCT in patients with renal impairment (GFR <60 mL/min/1.73 m^2).

7.5 Digoxin

When telmisartan was co-administered with digoxin, median increases in digoxin peak plasma concentration (49%) and in trough concentration (20%) were observed. Monitor digoxin levels in patients taking concomitant MICARDIS HCT and digoxin.

7.6 Antidiabetic Drugs (Oral Agents and Insulin)

Dosage adjustment of antidiabetic drugs may be required when co-administered with hydrochlorothiazide.

7.7 Cholestyramine and Colestipol Resins

Absorption of hydrochlorothiazide is impaired in the presence of anionic exchange resins. Stagger the dosage of hydrochlorothiazide and the resin such that hydrochlorothiazide is administered at least 4 hours before or 4 to 6 hours after the administration of the resin.

8 USE IN SPECIFIC POPULATIONS

8.1 Pregnancy

Risk Summary

MICARDIS HCT can cause fetal harm when administered to a pregnant woman. Use of drugs that act on the renin-angiotensin system during the second and third trimesters of pregnancy reduces fetal renal function and increases fetal and neonatal morbidity and death (see Clinical Considerations). Most epidemiologic studies examining fetal abnormalities after exposure to antihypertensive use in the first trimester have not distinguished drugs affecting the renin-angiotensin system from other antihypertensive agents. Studies in rats and rabbits with telmisartan showed fetotoxicity only at maternally toxic doses (see Data). When pregnancy is detected, discontinue MICARDIS HCT as soon as possible.

The estimated background risk of major birth defects and miscarriage for the indicated population is unknown. All pregnancies have a background risk of birth defect, loss, or other adverse outcomes. In the U.S. general population, the estimated background risk of major birth defects and miscarriage in clinically recognized pregnancies is 2% to 4% and 15% to 20%, respectively.

Clinical Considerations

Disease-associated maternal and/or embryo/fetal risk

Hypertension in pregnancy increases the maternal risk for pre-eclampsia, gestational diabetes, premature delivery, and delivery complications (e.g., need for cesarean section, and post-partum hemorrhage). Hypertension increases the fetal risk for intrauterine growth restriction and intrauterine death. Pregnant women with hypertension should be carefully monitored and managed accordingly.

Fetal/Neonatal adverse reactions

Telmisartan

Use of drugs that act on the RAS in the second and third trimesters of pregnancy can result in the following: oligohydramnios, reduced fetal renal function leading to anuria and renal failure, fetal lung hypoplasia, skeletal deformations, including skull hypoplasia, hypotension, and death. In the unusual case that there is no appropriate alternative to therapy with drugs affecting the renin-angiotensin system for a particular patient, apprise the mother of the potential risk to the fetus.

In patients taking MICARDIS HCT during pregnancy, perform serial ultrasound examinations to assess the intra-amniotic environment. Fetal testing may be appropriate, based on the week of gestation. If oligohydramnios is observed, discontinue MICARDIS HCT, unless it is considered lifesaving for the mother. Patients and physicians should be aware, however, that oligohydramnios may not appear until after the fetus has sustained irreversible injury.

Closely observe infants with histories of in utero exposure to MICARDIS HCT for hypotension, oliguria, and hyperkalemia. If oliguria or hypotension occurs, support blood pressure and renal perfusion. Exchange transfusions or dialysis may be required as a means of reversing hypotension and replacing renal function [see Use in Specific Populations (8.4)].

Hydrochlorothiazide

Thiazides cross the placenta, and use of thiazides during pregnancy is associated with a risk of fetal or neonatal jaundice, thrombocytopenia, and possible other adverse reactions that have occurred in adults.

Data

Animal Data

MICARDIS HCT

A developmental toxicity study was performed in rats with telmisartan/hydrochlorothiazide doses of 3.2/1.0, 15/4.7, 50/15.6, and 0/15.6 mg/kg/day. Although the two higher dose combinations appeared to be more toxic (significant decrease in body weight gain) to the dams than either drug alone, there did not appear to be an increase in toxicity to the developing embryos.

Telmisartan

No teratogenic effects were observed when telmisartan was administered to pregnant rats at oral doses of up to 50 mg/kg/day and to pregnant rabbits at oral doses of up to 45 mg/kg/day. In rabbits, embryo lethality associated with maternal toxicity (reduced body weight gain and food consumption) was observed at 45 mg/kg/day (approximately 12 times the maximum recommended human dose [MRHD] of 80 mg on a mg/m^2 basis). In rats, maternally toxic (reduced body weight gain and food consumption) telmisartan doses of 15 mg/kg/day (approximately 1.9 times the MRHD on a mg/m^2 basis), administered during late gestation and lactation, were observed to produce adverse effects in neonates, including reduced viability, low birth weight, delayed maturation, and decreased weight gain. The no-observed-effect doses for developmental toxicity in rats and rabbits, 5 and 15 mg/kg/day, respectively, are approximately 0.64 and 3.7 times, respectively, on a mg/m^2 basis, the MRHD of telmisartan (80 mg/day).

Hydrochlorothiazide

Studies in which hydrochlorothiazide was administered to pregnant mice and rats during their respective periods of major organogenesis at doses up to 3000 and 1000 mg/kg/day, respectively (about 600 and 400 times the MRHD), provided no evidence of harm to the fetus.

Thiazides can cross the placenta, and concentrations reached in the umbilical vein approach those in the maternal plasma. Hydrochlorothiazide, like other diuretics, can cause placental hypoperfusion. It accumulates in the amniotic fluid, with reported concentrations up to 19 times that in umbilical vein plasma. Use of thiazides during pregnancy is associated with a risk of fetal or neonatal jaundice or thrombocytopenia. Since they do not prevent or alter the course of EPH (Edema, Proteinuria, Hypertension) gestosis (pre-eclampsia), these drugs should not be used to treat hypertension in pregnant women. The use of hydrochlorothiazide for other indications (e.g., heart disease) in pregnancy should be avoided.

8.2 Lactation

Risk Summary

There is no information regarding the presence of MICARDIS HCT or telmisartan in human milk, the effects on the breastfed infant or the effects on milk production. Limited published studies report that hydrochlorothiazide is present in human milk. However, there is insufficient information to determine the effects of hydrochlorothiazide on the breastfed infant or the effects of hydrochlorothiazide on milk production. Telmisartan is present in the milk of lactating rats (see Data). Because of the potential for serious adverse reactions in the breastfed infant including hypotension, hyperkalemia and renal impairment, advise a nursing woman not to breastfeed during treatment with MICARDIS HCT.

Data

Telmisartan was present in the milk of lactating rats at concentrations 1.5 to 2 times those found in plasma from 4 to 8 hours after administration.

8.4 Pediatric Use

Safety and effectiveness of MICARDIS HCT in pediatric patients have not been established.

Neonates with a history of in utero exposure to MICARDIS HCT:

If oliguria or hypotension occurs, support blood pressure and renal perfusion. Exchange transfusions or dialysis may be required as means of reversing hypotension and/or substituting for disordered renal function.

8.5 Geriatric Use

In the controlled clinical trials (n=1017), approximately 20% of patients treated with telmisartan/hydrochlorothiazide were 65 years of age or older, and 5% were 75 years of age or older. No overall differences in effectiveness and safety of telmisartan/hydrochlorothiazide were observed in these patients compared to younger patients. Other reported clinical experience has not identified differences in responses between the elderly and younger patients, but greater sensitivity of some older individuals cannot be ruled out. In general, dose selection for an elderly patient should be cautious, usually starting at the low end of the dosing range, reflecting the greater frequency of decreased hepatic, renal or cardiac function and of concomitant diseases or other drug therapy.

8.6 Use in Patients with Hepatic Impairment

Patients with biliary obstructive disorders or hepatic insufficiency should initiate treatment under close medical supervision using the 40 mg/12.5 mg combination.

Telmisartan

As the majority of telmisartan is eliminated by biliary excretion, patients with biliary obstructive disorders or hepatic insufficiency can be expected to have reduced clearance and higher blood levels.

Hydrochlorothiazide

Minor alterations of fluid and electrolyte balance may precipitate hepatic coma in patients with impaired hepatic function or progressive liver disease.

8.7 Use in Patients with Renal Impairment

Safety and effectiveness of MICARDIS HCT in patients with severe renal impairment (CrCl ≤30 mL/min) have not been established. In patients with severe renal impairment, MICARDIS HCT tablets are not recommended. No dose adjustment is required in patients with mild (CrCl 60 to 90 mL/min) or moderate (CrCl 30 to 60 mL/min) renal impairment.

10 OVERDOSAGE

Telmisartan

Limited data are available with regard to overdosage of telmisartan in humans. The most likely manifestations of overdosage with telmisartan are hypotension, dizziness, and tachycardia; bradycardia could occur from parasympathetic (vagal) stimulation. If symptomatic hypotension should occur, supportive treatment should be instituted. Telmisartan is not removed by hemofiltration and is not dialyzable.

Hydrochlorothiazide

The most common signs and symptoms observed in patients with a hydrochlorothiazide overdose are those caused by electrolyte depletion (hypokalemia, hypochloremia, hyponatremia) and dehydration resulting from excessive diuresis. If digitalis has also been administered, hypokalemia may accentuate cardiac arrhythmias. The degree to which hydrochlorothiazide is removed by hemodialysis has not been established. The oral LD50 of hydrochlorothiazide is greater than 10 g/kg in both mice and rats.

11 DESCRIPTION

MICARDIS HCT tablets are a combination of telmisartan, an orally active angiotensin II antagonist acting on the AT1 receptor subtype, and hydrochlorothiazide, a thiazide diuretic.

Telmisartan, a non-peptide molecule, is chemically described as 4'-[(1,4'-dimethyl-2'-propyl[2,6'-bi-1H-benzimidazol]-1'-yl)methyl]-[1,1'-biphenyl]-2-carboxylic acid. Its empirical formula is C33H30N4O2, its molecular weight is 514.63, and its structural formula is:

Telmisartan is a white to slightly yellowish solid. It is practically insoluble in water and in the pH range of 3 to 9, sparingly soluble in strong acid (except insoluble in hydrochloric acid), and soluble in strong base.

Hydrochlorothiazide is a white, or practically white, practically odorless, crystalline powder with a molecular weight of 297.74. It is slightly soluble in water, and freely soluble in sodium hydroxide solution. Hydrochlorothiazide is chemically described as 6-chloro-3,4-dihydro-2H-1,2,4-benzothiadiazine-7-sulfonamide 1,1-dioxide. Its empirical formula is C7H8ClN3O4S2, and its structural formula is:

MICARDIS HCT tablets are formulated for oral administration in three combinations of 40 mg/12.5 mg, 80 mg/12.5 mg, and 80 mg/25 mg telmisartan and hydrochlorothiazide, respectively. The tablets contain the following inactive ingredients: sodium hydroxide, meglumine, povidone, sorbitol, magnesium stearate, lactose monohydrate, microcrystalline cellulose, maize starch, and sodium starch glycolate. As coloring agents, the 40 mg/12.5 mg and 80 mg/12.5 mg tablets contain ferric oxide red, and the 80 mg/25 mg tablets contain ferric oxide yellow. MICARDIS HCT tablets are hygroscopic and require protection from moisture.

12 CLINICAL PHARMACOLOGY

12.1 Mechanism of Action

MICARDIS HCT

MICARDIS HCT is a combination of two drugs with antihypertensive properties: a thiazide diuretic, hydrochlorothiazide, and an angiotensin II receptor blocker (ARB), telmisartan.

Telmisartan

Angiotensin II is formed from angiotensin I in a reaction catalyzed by angiotensin-converting enzyme (ACE, kininase II). Angiotensin II is the principal pressor agent of the renin-angiotensin system, with effects that include vasoconstriction, stimulation of synthesis and release of aldosterone, cardiac stimulation, and renal reabsorption of sodium. Telmisartan blocks the vasoconstrictor and aldosterone-secreting effects of angiotensin II by selectively blocking the binding of angiotensin II to the AT1 receptor in many tissues, such as vascular smooth muscle and the adrenal gland. Its action is therefore independent of the pathways for angiotensin II synthesis.

There is also an AT2 receptor found in many tissues, but AT2 is not known to be associated with cardiovascular homeostasis. Telmisartan has much greater affinity (>3,000-fold) for the AT1 receptor than for the AT2 receptor.

Telmisartan does not inhibit ACE (kininase II) nor does it bind to or block other hormone receptors or ion channels known to be important in cardiovascular regulation.

Blockade of the angiotensin II receptor inhibits the negative regulatory feedback of angiotensin II on renin secretion, but the resulting increased plasma renin activity and angiotensin II circulating levels do not overcome the effect of telmisartan on blood pressure.

Hydrochlorothiazide

Hydrochlorothiazide is a thiazide diuretic. Thiazides affect the renal tubular mechanisms of electrolyte reabsorption, directly increasing excretion of sodium salt and chloride in approximately equivalent amounts. Indirectly, the diuretic action of hydrochlorothiazide reduces plasma volume, with consequent increases in plasma renin activity, increases in aldosterone secretion, increases in urinary potassium loss, and decreases in serum potassium. The renin-aldosterone link is mediated by angiotensin II, so co-administration of an ARB tends to reverse the potassium loss associated with these diuretics. The mechanism of the antihypertensive effect of thiazides is not fully understood.

12.2 Pharmacodynamics

Telmisartan

In normal volunteers, a dose of telmisartan 80 mg inhibited the pressor response to an intravenous infusion of angiotensin II by approximately 90% at peak plasma concentrations with approximately 40% inhibition persisting for 24 hours.

Plasma concentration of angiotensin II and plasma renin activity increased in a dose-dependent manner after single administration of telmisartan to healthy subjects and repeated administration to hypertensive patients. The once-daily administration of up to 80 mg telmisartan to healthy subjects did not influence plasma aldosterone concentrations. In multiple dose studies with hypertensive patients, there were no clinically significant changes in electrolytes (serum potassium or sodium) or in metabolic function (including serum levels of cholesterol, triglycerides, HDL, LDL, glucose, or uric acid).

The antihypertensive effects of telmisartan have been studied in six placebo-controlled clinical trials including a total of 1773 patients with mild to moderate hypertension (diastolic blood pressure of 95 to 114 mmHg), 1031 of whom were treated with telmisartan. Following once-daily administration of telmisartan, the magnitude of blood pressure reduction from baseline after placebo subtraction was approximately (SBP/DBP) 6-8/6 mmHg for 20 mg, 9-13/6-8 mmHg for 40 mg, and 12-13/7-8 mmHg for 80 mg. Larger doses (up to 160 mg) did not appear to cause a further decrease in blood pressure.

The onset of antihypertensive activity occurs within 3 hours, with a maximal reduction by approximately 4 weeks. At doses of 20, 40, and 80 mg, the antihypertensive effect of once-daily administration of telmisartan was maintained for the full 24-hour dose interval.

In 30 hypertensive patients with normal renal function treated for 8 weeks with telmisartan 80 mg or telmisartan 80 mg in combination with hydrochlorothiazide 12.5 mg, there were no clinically significant changes from baseline in renal blood flow, glomerular filtration rate, filtration fraction, renovascular resistance, or creatinine clearance.

Hydrochlorothiazide

After oral administration of hydrochlorothiazide, diuresis begins within 2 hours, peaks in about 4 hours, and lasts approximately 6 to 12 hours.

Drug Interactions

Hydrochlorothiazide

Alcohol, barbiturates, or narcotics: Potentiation of orthostatic hypotension may occur.

Skeletal muscle relaxants: Possible increased responsiveness to muscle relaxants such as curare derivatives.

Corticosteroids, ACTH: Intensified electrolyte depletion, particularly hypokalemia.

Pressor amines (e.g., norepinephrine): Possible decreased response to pressor amines but not sufficient to preclude their use.

12.3 Pharmacokinetics

Telmisartan

Absorption:

Following oral administration, peak concentrations (Cmax) of telmisartan are reached in 0.5 to 1 hour after dosing. Food slightly reduces the bioavailability of telmisartan, with a reduction in the area under the plasma concentration-time curve (AUC) of approximately 6% with 40 mg and approximately 20% after a 160 mg dose. MICARDIS HCT can be administered with or without food. The absolute bioavailability of telmisartan is dose dependent. At 40 mg and 160 mg, the bioavailability was 42% and 58%, respectively. The pharmacokinetics of telmisartan with orally administered MICARDIS are nonlinear over the dose range 20 mg to 160 mg, with greater than proportional increases of plasma concentrations (Cmax and AUC) with increasing doses. Telmisartan shows bi-exponential decay kinetics with a terminal elimination half-life of approximately 24 hours. Trough plasma concentrations of telmisartan with once-daily dosing are approximately 10% to 25% of peak plasma concentrations. Telmisartan has an accumulation index in plasma of 1.5 to 2.0 upon repeated once-daily dosing.

Distribution:

Telmisartan is highly bound to plasma proteins (>99.5%), mainly albumin and α1-acid glycoprotein. Plasma protein binding is constant over the concentration range achieved with recommended doses. The volume of distribution for telmisartan is approximately 500 liters, indicating additional tissue binding.

Metabolism:

Telmisartan is metabolized by conjugation to form a pharmacologically inactive acyl glucuronide; the glucuronide of the parent compound is the only metabolite that has been identified in human plasma and urine. After a single dose, the glucuronide represents approximately 11% of the measured radioactivity in plasma. The cytochrome P450 isoenzymes are not involved in the metabolism of telmisartan.

Elimination:

Following either intravenous or oral administration of ^14C-labeled telmisartan, most of the administered dose (>97%) was eliminated unchanged in feces via biliary excretion; only minute amounts were found in the urine (0.91% and 0.49% of total radioactivity, respectively).

Total plasma clearance of telmisartan is >800 mL/min. Terminal half-life and total clearance appear to be independent of dose.

Hydrochlorothiazide

Hydrochlorothiazide is not metabolized but is eliminated rapidly by the kidney. When plasma levels have been followed for at least 24 hours, the plasma half-life has been observed to vary between 5.6 and 14.8 hours. At least 61% of the oral dose is eliminated unchanged within 24 hours. Hydrochlorothiazide crosses the placental but not the blood-brain barrier and is excreted in breast milk.

Specific Populations

Telmisartan

Renal Insufficiency: Telmisartan is not removed from blood by hemofiltration and is not dialyzable [see Warnings and Precautions (5.3) and Use in Specific Populations (8.7)].

Hepatic Insufficiency: In patients with hepatic insufficiency, plasma concentrations of telmisartan are increased, and absolute bioavailability approaches 100% [see Use in Specific Populations (8.6)].

Gender: Plasma concentrations of telmisartan are generally 2 to 3 times higher in females than in males. In clinical trials, however, no significant increases in blood pressure response or in the incidence of orthostatic hypotension were found in women. No dosage adjustment is necessary.

Geriatric Patients: The pharmacokinetics of telmisartan do not differ between the elderly and those younger than 65 years of age.

Drug Interaction Studies

Telmisartan

Ramipril: Co-administration of telmisartan 80 mg once daily and ramipril 10 mg once daily to healthy subjects increases steady-state Cmax and AUC of ramipril 2.3- and 2.1-fold, respectively, and Cmax and AUC of ramiprilat 2.4- and 1.5-fold, respectively. In contrast, Cmax and AUC of telmisartan decrease by 31% and 16%, respectively. When co-administering telmisartan and ramipril, the response may be greater because of the possibly additive pharmacodynamic effects of the combined drugs, and also because of the increased exposure to ramipril and ramiprilat in the presence of telmisartan.

Other Drugs: Co-administration of telmisartan did not result in a clinically significant interaction with acetaminophen, amlodipine, glyburide, simvastatin, hydrochlorothiazide, warfarin, or ibuprofen. Telmisartan is not metabolized by the cytochrome P450 system and had no effects in vitro on cytochrome P450 enzymes, except for some inhibition of CYP2C19. Telmisartan is not expected to interact with drugs that inhibit cytochrome P450 enzymes; it is also not expected to interact with drugs metabolized by cytochrome P450 enzymes, except for possible inhibition of the metabolism of drugs metabolized by CYP2C19.

13 NONCLINICAL TOXICOLOGY

13.1 Carcinogenesis, Mutagenesis, Impairment of Fertility

Telmisartan and Hydrochlorothiazide

No carcinogenicity, mutagenicity, or fertility studies have been conducted with the combination of telmisartan and hydrochlorothiazide.

Telmisartan

There was no evidence of carcinogenicity when telmisartan was administered in the diet to mice and rats for up to 2 years. The highest doses administered to mice (1000 mg/kg/day) and rats (100 mg/kg/day) are, on a mg/m^2 basis, about 59 and 13 times, respectively, the maximum recommended human dose (MRHD) of telmisartan. These same doses have been shown to provide average systemic exposures to telmisartan >100 times and >25 times, respectively, the systemic exposure in humans receiving the MRHD of telmisartan (80 mg/day).

Genotoxicity assays did not reveal any telmisartan-related effects at either the gene or chromosome level. These assays included bacterial mutagenicity tests with Salmonella and E. coli (Ames), a gene mutation test with Chinese hamster V79 cells, a cytogenetic test with human lymphocytes, and a mouse micronucleus test.

No drug-related effects on the reproductive performance of male and female rats were noted at 100 mg/kg/day (the highest dose administered), about 13 times, on a mg/m^2 basis, the MRHD of telmisartan. This dose in the rat resulted in an average systemic exposure (telmisartan AUC as determined on day 6 of pregnancy) at least 50 times the average systemic exposure in humans at the MRHD (80 mg/day).

Hydrochlorothiazide

Two-year feeding studies in mice and rats conducted under the auspices of the National Toxicology Program (NTP) uncovered no evidence of a carcinogenic potential of hydrochlorothiazide in female mice (at doses of up to approximately 600 mg/kg/day) or in male and female rats (at doses of up to approximately 100 mg/kg/day). The NTP, however, found equivocal evidence for hepatocarcinogenicity in male mice.

Hydrochlorothiazide was not genotoxic in vitro in the Ames mutagenicity assay of Salmonella typhimurium strains TA 98, TA 100, TA 1535, TA 1537, and TA 1538 and in the Chinese Hamster Ovary (CHO) test for chromosomal aberrations, or in vivo in assays using mouse germinal cell chromosomes, Chinese hamster bone marrow chromosomes, and the Drosophila sex-linked recessive lethal trait gene. Positive test results were obtained in the in vitro CHO Sister Chromatid Exchange (clastogenicity) assay, in the Mouse Lymphoma Cell (mutagenicity) assay, and in the Aspergillus nidulans non-disjunction assay.

Hydrochlorothiazide had no adverse effects on the fertility of mice and rats of either sex in studies wherein these species were exposed, via their diet, to doses of up to 100 and 4 mg/kg, respectively, prior to mating and throughout gestation.

14 CLINICAL STUDIES

Telmisartan and Hydrochlorothiazide

In controlled clinical trials with more than 2500 hypertensive patients, 1017 patients were exposed to telmisartan (20 mg to 160 mg) and concomitant hydrochlorothiazide (6.25 mg to 25 mg). These trials included one factorial trial (Study 1) with combinations of telmisartan (20 mg, 40 mg, 80 mg, 160 mg, or placebo) and hydrochlorothiazide (6.25 mg, 12.5 mg, 25 mg, and placebo). The factorial trial randomized 818 patients, including 493 (60%) males; 596 (73%) Non-Black and 222 (27%) Blacks; and 143 (18%) ≥65 years of age (median age was 53 years old). The mean supine blood pressure at baseline for the total population was 154/101 mmHg.

The combination of telmisartan and hydrochlorothiazide resulted in additive placebo-adjusted decreases in systolic and diastolic blood pressures at trough of 16-21/9-11 mmHg for doses between 40 mg/12.5 mg and 80 mg/25 mg, compared with 9-13/7-8 mmHg for telmisartan 40 mg to 80 mg monotherapy and 4/4 mmHg for hydrochlorothiazide 12.5 mg monotherapy. The antihypertensive effect was independent of age or gender. There was essentially no change in heart rate in patients treated with the combination of telmisartan and hydrochlorothiazide in the placebo-controlled trial.

Four other studies of hypertensive patients of at least six months' duration allowed add-on of hydrochlorothiazide for patients who either were not adequately controlled on the randomized telmisartan monotherapy dose or had not achieved adequate blood pressure response after completing the up-titration of telmisartan. In active-controlled studies, the addition of 12.5 mg hydrochlorothiazide to titrated doses of telmisartan in patients who did not achieve or maintain adequate response with telmisartan monotherapy further reduced systolic and diastolic blood pressures.

16 HOW SUPPLIED/STORAGE AND HANDLING

MICARDIS HCT is available in three strengths as biconvex two-layered, oblong-shaped, uncoated tablets containing telmisartan and hydrochlorothiazide:

- 40 mg/12.5 mg tablet: red and white (may contain red specks) marked with the Boehringer Ingelheim company symbol and "H4"; individually blister-sealed in cartons of 30 tablets as 3 × 10 cards (NDC 0597-0043-37)
- 80 mg/12.5 mg tablet: red and white (may contain red specks) marked with the Boehringer Ingelheim company symbol and "H8"; individually blister-sealed in cartons of 30 tablets as 3 × 10 cards (NDC 0597-0044-37)
- 80 mg/25 mg tablet: yellow and white (may contain yellow specks) marked with the Boehringer Ingelheim company symbol and "H9"; individually blister-sealed in cartons of 30 tablets as 3 × 10 cards (NDC 0597-0042-37)

Storage

Store at 20°C to 25°C (68°F to 77°F); excursions permitted to 15°C to 30°C (59°F to 86°F) [see USP Controlled Room Temperature]. Tablets should not be removed from blisters until immediately before administration.

17 PATIENT COUNSELING INFORMATION

Advise the patient to read the FDA-approved patient labeling (Patient Information).

Pregnancy

Advise female patients of childbearing age about the consequences of exposure to MICARDIS HCT during pregnancy. Discuss treatment options with women planning to become pregnant. Tell patients to report pregnancies to their physicians as soon as possible [see Warnings and Precautions (5.1) and Use in Specific Populations (8.1)].

Lactation

Advise nursing women not to breastfeed during treatment with MICARDIS HCT [see Use in Specific Populations (8.2)].

Symptomatic Hypotension and Syncope

Advise patients that lightheadedness can occur, especially during the first days of therapy, and to report it to their healthcare provider. Inform patients that inadequate fluid intake, excessive perspiration, diarrhea, or vomiting can lead to an excessive fall in blood pressure, with the same consequences of lightheadedness and possible syncope. Advise patients to contact their healthcare provider if syncope occurs [see Warnings and Precautions (5.2)].

Potassium Supplements

Advise patients not to use potassium supplements or salt substitutes that contain potassium without consulting the prescribing healthcare provider [see Warnings and Precautions (5.4) and Drug Interactions (7.1)].

Acute Myopia and Secondary Angle-Closure Glaucoma

Advise patients to discontinue MICARDIS HCT and seek immediate medical attention if they experience symptoms of Acute Myopia or Secondary Angle-Closure Glaucoma [see Warnings and Precautions (5.6)].

Non-melanoma Skin Cancer

Instruct patients taking hydrochlorothiazide to protect skin from the sun and undergo regular skin cancer screening.

Distributed by:
Boehringer Ingelheim Pharmaceuticals, Inc.
Ridgefield, CT 06877 USA

Licensed from:
Boehringer Ingelheim International GmbH
Ingelheim, Germany

Copyright © 2022 Boehringer Ingelheim International GmbH
ALL RIGHTS RESERVED

MICARDIS® is a registered trademark of and used under license from Boehringer Ingelheim International GmbH.

Boehringer Ingelheim Pharmaceuticals, Inc. either owns or uses the ONTARGET® trademark under license.

The other brands listed are trademarks of their respective owners and are not trademarks of Boehringer Ingelheim Pharmaceuticals, Inc.

COL10674AL272022
SPL10694A

Patient Information MICARDIS® HCT (my-CAR-dis HCT) (telmisartan and hydrochlorothiazide tablets)

Read this Patient Information before you start taking MICARDIS HCT tablets and each time you get a refill. There may be new information. This information does not take the place of talking to your doctor about your medical condition or your treatment.

What is the most important information I should know about MICARDIS HCT tablets?

MICARDIS HCT can cause harm or death to an unborn baby. Talk to your doctor about other ways to lower your blood pressure if you plan to become pregnant. If you get pregnant while taking MICARDIS HCT, tell your doctor right away.

What is MICARDIS HCT?

MICARDIS HCT is a prescription medicine used to treat high blood pressure (hypertension). MICARDIS HCT contains:

- telmisartan, an angiotensin receptor blocker (ARB)
- hydrochlorothiazide, a water pill or diuretic

Your doctor may prescribe other medicines for you to take along with MICARDIS HCT to treat your high blood pressure.

It is not known if MICARDIS HCT is safe and effective in children.

Do not take MICARDIS HCT tablets if you:

- have low or no urine output
- are allergic (hypersensitive) to the active ingredients (telmisartan or hydrochlorothiazide) or any of the other ingredients listed at the end of this leaflet

What should I tell my doctor before using MICARDIS HCT tablets?

Before you take MICARDIS HCT tablets, tell your doctor if you:

- are pregnant or are planning to become pregnant. See "What is the most important information I should know about MICARDIS HCT tablets?"
- are breast-feeding or plan to breast-feed. MICARDIS HCT can pass into your breast milk and may harm your baby. You and your doctor should decide if you will take MICARDIS HCT or breast-feed. You should not do both. Talk with your doctor about the best way to feed your baby if you take MICARDIS HCT tablets.
- have been told that you have abnormal body salt (electrolytes) levels in your blood
- have liver problems
- have asthma or history of asthma
- have lupus
- have diabetes
- have kidney problems
- have any other medical conditions

Tell your doctor about all the medicines you take, including prescription and non-prescription medicines, vitamins, and herbal supplements. Also, tell your doctor if you drink alcohol.

MICARDIS HCT may affect the way other medicines work, and other medicines may affect how MICARDIS HCT works. Especially tell your doctor if you take:

- aliskiren
- digoxin (Lanoxin®)
- lithium (Lithobid®, lithium carbonate, lithium citrate)
- other medicines used to treat your high blood pressure or a heart problem
- water pills (diuretic)
- aspirin or other non-steroidal anti-inflammatory drugs (NSAIDs)
- potassium supplements or a salt substitute containing potassium
- medicine used to treat diabetes, including insulin
- narcotic pain medicines
- sleeping pills
- steroid medicine or Adrenocorticotrophic Hormone (ACTH)
- barbiturates
- certain cholesterol lowering medicines (resins that are used for cholesterol reduction, e.g., cholestyramine and colestipol resins)

Ask your doctor if you are not sure if you are taking one of the medicines listed above.

Know the medicines you take. Keep a list of them and show it to your doctor or pharmacist when you get a new medicine.

How should I take MICARDIS HCT tablets?

- Take MICARDIS HCT tablets exactly as your doctor tells you to take it.
- Your doctor will tell you how much MICARDIS HCT to take and when to take it.
- Do not change your dose unless your doctor tells you to.
- Take MICARDIS HCT once each day.
- Take MICARDIS HCT tablets with or without food.
- If you take too much MICARDIS HCT, call your doctor, or go to the nearest hospital emergency room right away.
- Read the "How to open the blister" at the end of this leaflet before you use MICARDIS HCT. Talk with your doctor if you do not understand the instructions.

What are the possible side effects of MICARDIS HCT tablets?

MICARDIS HCT tablets may cause serious side effects, including:

- Injury or death to your unborn baby. See "What is the most important information I should know about MICARDIS HCT tablets?"
- Low blood pressure (hypotension) is most likely to happen if you also:
  - take water pills (diuretics)
  - are on a low-salt diet
  - get dialysis treatments
  - have heart problems
  - get sick with vomiting or diarrhea
  - do not drink enough fluids
  - sweat a lot
  If you feel faint or dizzy, lie down and call your doctor right away.
- Kidney problems, which may get worse if you already have kidney disease. You may have changes in your kidney test results, and you may need a lower dose of MICARDIS HCT tablets. Call your doctor if you get:
  - swelling in your feet, ankles, or hands
  - unexplained weight gain
  Call your doctor right away if you get any of the symptoms listed above.
- Liver problems, which may get worse in people who already have liver problems and take MICARDIS HCT.
- Eye problems. One of the medicines in MICARDIS HCT can cause eye problems that may lead to vision loss. Symptoms of eye problems can happen within hours to weeks of starting MICARDIS HCT. Tell your doctor right away if you have:
  - decrease in vision
  - eye pain
- Allergic reactions. Tell your doctor right away if you get any of these symptoms:
  - swelling of the face, tongue, throat
  - difficulty breathing
- Worsening of lupus. Tell your doctor if your lupus gets worse or becomes active while taking MICARDIS HCT.
- Change in body salts (electrolytes) level in your blood and fluid problems. Your doctor may do tests to check your blood. Call your doctor right away if you have:

- dry mouth
- thirst
- tiredness
- sleepiness
- restlessness
- confusion

- seizures
- fast heartbeats
- weakness
- muscle pain or cramps
- very low urine output
- nausea or vomiting

- Skin Cancer. One of the medicines in MICARDIS HCT may increase your risk of getting non-melanoma skin cancer. Protect your skin from the sun and undergo regular skin cancer screening when taking MICARDIS HCT.

The most common side effects of MICARDIS HCT tablets include:

- upper respiratory tract infections, including sinus pain/congestion and sore throat
- dizziness
- feeling tired
- flu-like symptoms
- back pain
- diarrhea
- nausea

These are not all the possible side effects with MICARDIS HCT tablets. Tell your doctor if you have any side effect that bothers you or that does not go away. Call your doctor for medical advice about side effects. You may report side effects to FDA at 1-800-FDA-1088.

How should I store MICARDIS HCT tablets?

- Store MICARDIS HCT tablets at room temperature between 68°F to 77°F (20°C to 25°C).
- Do not remove MICARDIS HCT tablets from blisters until right before you take them.

Keep MICARDIS HCT tablets and all medicines out of the reach of children.

General information about MICARDIS HCT tablets:

Medicines are sometimes prescribed for purposes other than those listed in a Patient Information leaflet. Do not use MICARDIS HCT tablets for a condition for which it was not prescribed. Do not give MICARDIS HCT tablets to other people, even if they have the same condition you have. It may harm them.

This Patient Information leaflet summarizes the most important information about MICARDIS HCT tablets. If you would like more information, talk with your doctor. You can ask your pharmacist or doctor for information about MICARDIS HCT tablets that is written for health professionals.

For current prescribing information, scan the code or call Boehringer Ingelheim Pharmaceuticals, Inc. at 1-800-542-6257.

What are the ingredients in MICARDIS HCT tablets?

Active Ingredients: telmisartan and hydrochlorothiazide

Inactive Ingredients: sodium hydroxide, meglumine, povidone, sorbitol, magnesium stearate, lactose monohydrate, microcrystalline cellulose, maize starch, and sodium starch glycolate

The 40 mg/12.5 mg and 80 mg/12.5 mg tablets also contain: ferric oxide red.

The 80 mg/25 mg tablets also contain: ferric oxide yellow.

What is high blood pressure (hypertension)?

Blood pressure is the force in your blood vessels when your heart beats and when your heart rests. You have high blood pressure when the force is too much. Medicines that lower your blood pressure lower your chance of having a stroke or heart attack.

High blood pressure makes the heart work harder to pump blood through the body and causes damage to the blood vessels. MICARDIS HCT tablets can help your blood vessels relax so your blood pressure is lower.

How to open the blister:

1. Tear (You may also use scissors to tear the blister apart)
2. Peel (Peel off the paper layer from the aluminum foil)
3. Push (Push the tablet through the aluminum foil)

This Patient Information has been approved by the U.S. Food and Drug Administration.

Distributed by:
Boehringer Ingelheim Pharmaceuticals, Inc.
Ridgefield, CT 06877 USA

Licensed from:
Boehringer Ingelheim International GmbH
Ingelheim, Germany

Copyright © 2022 Boehringer Ingelheim International GmbH
ALL RIGHTS RESERVED

MICARDIS® is a registered trademark of and used under license from Boehringer Ingelheim International GmbH.

Boehringer Ingelheim Pharmaceuticals, Inc. either owns or uses the ONTARGET® trademark under license.

The other brands listed are trademarks of their respective owners and are not trademarks of Boehringer Ingelheim Pharmaceuticals, Inc.

Revised: December 2022

COL10674AL272022
SPL10694A

PRINCIPAL DISPLAY PANEL - 40 mg/12.5 mg Tablet Blister Card Carton

NDC 0597-0043-37

Micardis® HCT
(telmisartan/
hydrochlorothiazide tablets)

40 mg/12.5 mg

Rx only

30 tablets - 3 blister cards of 10 tablets each.
Each tablet contains 40 mg of telmisartan and 12.5 mg of
hydrochlorothiazide.

Dosage: Read accompanying prescribing information.

Keep out of reach of children.

Important: Moisture sensitive tablets - do not remove
from blisters until immediately before administration.

Boehringer
Ingelheim

PRINCIPAL DISPLAY PANEL - 80 mg/12.5 mg Tablet Blister Card Carton

NDC 0597-0044-37

Micardis® HCT
(telmisartan/
hydrochlorothiazide tablets)

80 mg/12.5 mg

Rx only

30 tablets - 3 blister cards of 10 tablets each.
Each tablet contains 80 mg of telmisartan and 12.5 mg of
hydrochlorothiazide.

Dosage: Read accompanying prescribing information.

Keep out of reach of children.

Important: Moisture sensitive tablets - do not remove
from blisters until immediately before administration.

Boehringer
Ingelheim

PRINCIPAL DISPLAY PANEL - 80 mg/25 mg Tablet Blister Card Carton

NDC 0597-0042-37

Micardis® HCT
(telmisartan/
hydrochlorothiazide tablets)

80 mg/25 mg

Rx only

30 tablets - 3 blister cards of 10 tablets each.
Each tablet contains 80 mg of telmisartan and 25 mg of
hydrochlorothiazide.

Dosage: Read accompanying prescribing information.

Keep out of reach of children.

Important: Moisture sensitive tablets - do not remove
from blisters until immediately before administration.

Boehringer
Ingelheim